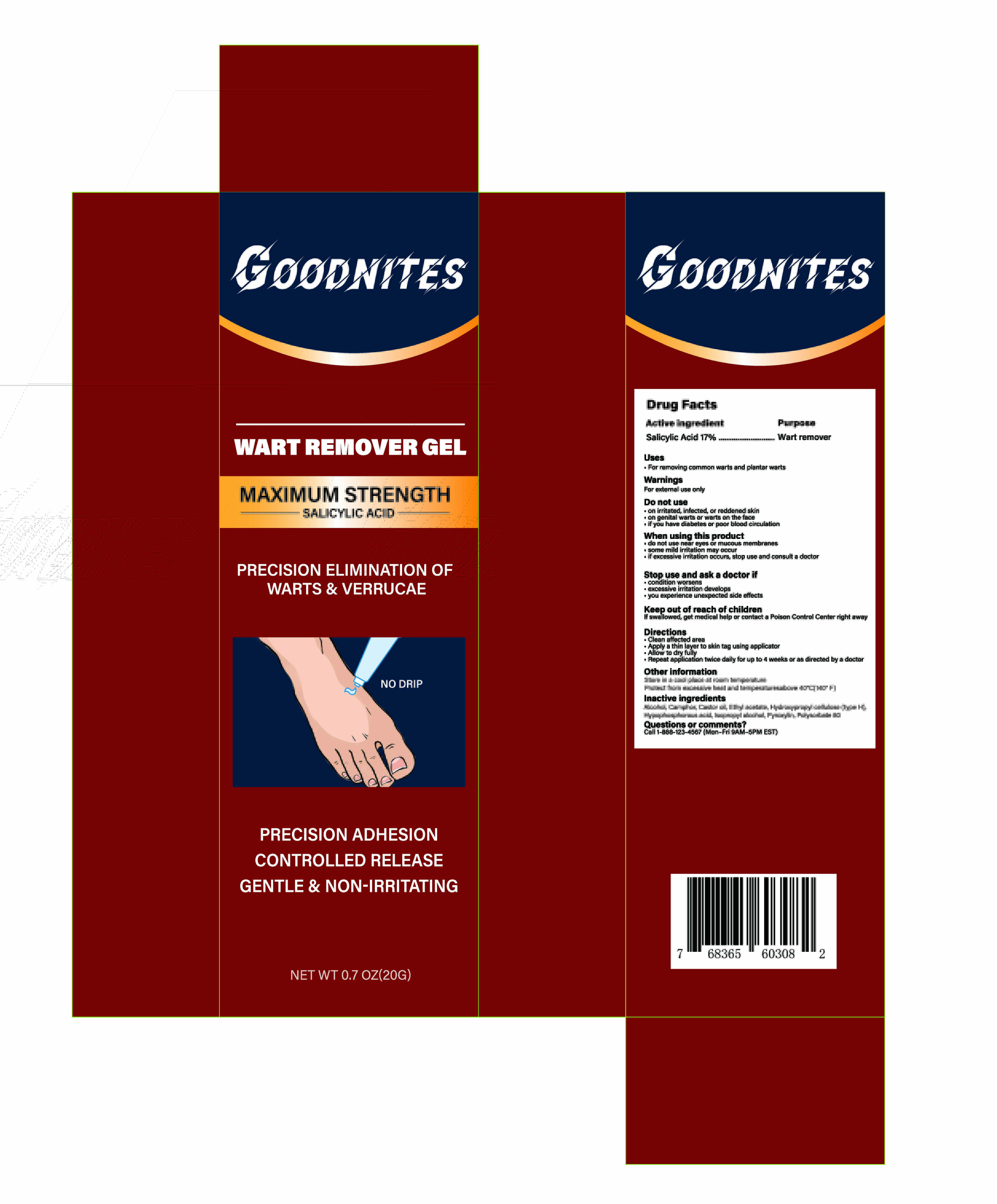 DRUG LABEL: Goodnites Wart Removal Gel
NDC: 85578-005 | Form: LIQUID
Manufacturer: Zhengzhou Hangrui Network Technology Co., Ltd.
Category: otc | Type: HUMAN OTC DRUG LABEL
Date: 20250627

ACTIVE INGREDIENTS: SALICYLIC ACID 0.17 g/1 mL
INACTIVE INGREDIENTS: ALCOHOL; CAMPHOR (NATURAL); CASTOR OIL; HYDROXYPROPYL CELLULOSE (1600000 WAMW); PYROXYLIN; POLYSORBATE 80; ETHYL ACETATE; HYPOPHOSPHOROUS ACID; ISOPROPYL ALCOHOL

85578-005 Goodnites Wart Removal Gel

ACTIVE INGREDIENT

Salicylic Acid 17%

PURPOSE

Wart remover

INDICATIONS AND USAGE

.For removing common warts and plantar warts

WARNINGS

For external use only

DO NOT USE

on irritated, infected, or reddened skin
on genital warts or warts on the face
if you have diabetes or poor blood circulation

do not use near eyes or mucous membranes
some mild irritation may occur
if excessive irritation occurs, stop use and consult a doctor

STOP USE

condition worsens
excessive irritation develops
you experience unexpected side effects

KEEP OUT OF REACH OF CHILDREN

If swallowed, get medical help or contact a Poison Control Center right away

DOSAGE AND ADMINISTRATION

Clean affected area
Apply a thin layer to skin tag using applicator.
Allow to dry fully
Repeat application twice daily for up to 4 weeks or as directed by a doctor

INACTIVE INGREDIENT

ALCOHOL
CAMPHOR (NATURAL)
CASTOR OIL
ETHYL ACETATE
HYDROXYPROPYL CELLULOSE (TYPE H)
HYPOPHOSPHOROUS ACID
ISOPROPYL ALCOHOL
PYROXYLIN
POLYSORBATE 80